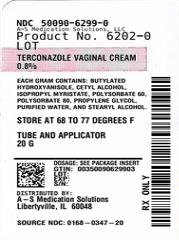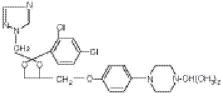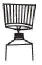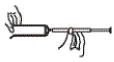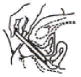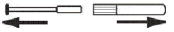 DRUG LABEL: Terconazole
NDC: 50090-6299 | Form: CREAM
Manufacturer: A-S Medication Solutions
Category: prescription | Type: HUMAN PRESCRIPTION DRUG LABEL
Date: 20230103

ACTIVE INGREDIENTS: TERCONAZOLE 8 mg/1 g
INACTIVE INGREDIENTS: butylated hydroxyanisole; cetyl alcohol; isopropyl myristate; polysorbate 60; polysorbate 80; propylene glycol; stearyl alcohol; water

Terconazole Vaginal Cream 0.8%

DESCRIPTION

Terconazole vaginal cream 0.8% is a white to off-white, water washable cream for intravaginal administration containing 0.8% of the antifungal agent terconazole, cis-1-[p-[[2-(2,4-Dichlorophenyl)-2-(1H-1,2,4-triazol-1-ylmethyl)-1,3-dioxolan-4-yl]methoxy]phenyl]-4-isopropylpiperazine, compounded in a cream base consisting of butylated hydroxyanisole, cetyl alcohol, isopropyl myristate, polysorbate 60, polysorbate 80, propylene glycol, stearyl alcohol, and purified water. The structural formula of terconazole is as follows:

Terconazole, a triazole derivative, is a white to almost white powder with a molecular weight of 532.47. It is insoluble in water; sparingly soluble in ethanol; and soluble in butanol.

CLINICAL PHARMACOLOGY

Following intravaginal administration of terconazole in humans, absorption ranged from 5-8% in three hysterectomized subjects and 12-16% in two non-hysterectomized subjects with tubal ligations.

Following daily intravaginal administration of 0.8% terconazole 40 mg (0.8% cream x 5 g) for seven days to normal humans, plasma concentrations were low and gradually rose to a daily peak (mean of 5.9 ng/mL or 0.006 mcg/mL) at 6.6 hours. Results from similar studies in patients with vulvovaginal candidiasis indicate that the slow rate of absorption, the lack of accumulation, and the mean peak plasma concentration of terconazole was not different from that observed in healthy women. The absorption characteristics of terconazole 0.8% in pregnant or non-pregnant patients with vulvovaginal candidiasis were also similar to those found in normal volunteers.

Following oral (30 mg) administration of ^14C-labelled terconazole, the harmonic half-life of elimination from the blood for the parent terconazole was 6.9 hours (range 4.0-11.3). Terconazole is extensively metabolized; the plasma AUC for terconazole compared to the AUC for total radioactivity was 0.6%. Total radioactivity was eliminated from the blood with a harmonic half-life of 52.2 hours (range 44-60). Excretion of radioactivity was both by renal (32-56%) and fecal (47-52%) routes.

In vitro, terconazole is highly protein bound (94.9%) and the degree of binding is independent of drug concentration.

Photosensitivity reactions were observed in some normal volunteers following repeated dermal application of terconazole 2.0% and 0.8% creams under conditions of filtered artificial ultraviolet light.

Photosensitivity reactions have not been observed in U.S. and foreign clinical trials in patients who were treated with terconazole suppositories or vaginal cream 0.8%.

Microbiology: Terconazole exhibits fungicidal activity in vitro against Candida albicans. Antifungal activity also has been demonstrated against other fungi. The MIC values of terconazole against most Lactobacillus spp. typically found in the human vagina were > 128 mcg/mL; therefore these beneficial bacteria are not affected by drug treatment.

The exact pharmacologic mode of action of terconazole is uncertain; however, it may exert its antifungal activity by the disruption of normal fungal cell membrane permeability. No resistance to terconazole has developed during successive passages of C. albicans.

INDICATIONS AND USAGE

Terconazole vaginal cream 0.8% is indicated for the local treatment of vulvovaginal candidiasis (moniliasis). As terconazole vaginal cream 0.8% is effective only for vulvovaginitis caused by the genus Candida, the diagnosis should be confirmed by KOH smears and/or cultures.

CONTRAINDICATIONS

Patients known to be hypersensitive to terconazole or to any of the components of the cream.

WARNINGS

None.

PRECAUTIONS

GENERAL PRECAUTIONS

General: Discontinue use and do not retreat with terconazole if sensitization, irritation, fever, chills or flu-like symptoms are reported during use.

LABORATORY TESTS

Laboratory Tests: If there is a lack of response to terconazole, appropriate microbiological studies (standard KOH smear and/or cultures) should be repeated to confirm the diagnosis and rule out other pathogens.

DRUG INTERACTIONS

Drug Interactions: The therapeutic effect of this product is not affected by oral contraceptive usage.

Carcinogenesis, Mutagenesis, Impairment of Fertility:

Carcinogenesis: Studies to determine the carcinogenic potential of terconazole have not been performed.

Mutagenicity: Terconazole was not mutagenic when tested in vitro for induction of microbial point mutations (Ames test), or for inducing cellular transformation, or in vivo for chromosome breaks (micronucleus test) or dominant lethal mutations in mouse germ cells.

Impairment of Fertility: No impairment of fertility occurred when female rats were administered terconazole orally up to 40 mg/kg/day for a three month period.

Pregnancy: Teratogenic Effects: Pregnancy Category C:

There was no evidence of teratogenicity when terconazole was administered orally up to 40 mg/kg/day (50x the recommended intravaginal human dose of the 0.8% vaginal cream formulation) in rats, or 20 mg/kg/day in rabbits, or subcutaneously up to 20 mg/kg/day in rats.

Dosages at or below 10 mg/kg/day produced no embryotoxicity; however there was a delay in fetal ossification at 10 mg/kg/day in rats. There was some evidence of embryotoxicity in rabbits and rats at 20-40 mg/kg. In rats, this was reflected as a decrease in litter size and number of viable young and reduced fetal weight. There was also delay in ossification and an increase incidence of skeletal variants.

The no-effect dose of 10 mg/kg/day resulted in a mean peak plasma level of terconazole in pregnant rats of 0.176 mcg/mL which exceeds by 30 times the mean peak plasma level (0.006 mcg/mL) seen in normal subjects after intravaginal administration of terconazole vaginal cream 0.8%. This safety assessment does not account for possible exposure of the fetus through direct transfer to terconazole from the irritated vagina by diffusion across amniotic membranes. Since terconazole is absorbed from the human vagina, it should not be used in the first trimester of pregnancy unless the physician considers it essential to the welfare of the patient.

NURSING MOTHERS

Nursing Mothers: It is not known whether this drug is excreted in human milk. Animal studies have shown that rat offspring exposed via the milk of treated (40 mg/kg/orally) dams showed decreased survival during the first few post-partum days, but overall pup weight and weight gain were comparable to or greater than controls throughout lactation. Because many drugs are excreted in human milk, and because of the potential for adverse reaction in nursing infants from terconazole, a decision should be made whether to discontinue nursing or to discontinue the drug, taking into account the importance of the drug to the mother.

PEDIATRIC USE

Pediatric Use: Safety and efficacy in children have not been established.

GERIATRIC USE

Geriatric Use: Clinical studies of terconazole vaginal cream did not include sufficient numbers of subjects aged 65 and over to determine whether they respond differently from younger subjects. Other reported clinical experience has not identified differences in responses between the elderly and younger patients.

ADVERSE REACTIONS

During controlled clinical studies conducted in the United States, patients with vulvovaginal candidiasis were treated with terconazole vaginal cream 0.8% for 3 days. Based on comparative analyses with placebo and a standard agent, the adverse experiences considered most likely related to terconazole vaginal cream 0.8% were headache (21% vs 16% with placebo) and dysmenorrhea (6% vs 2% with placebo). Genital complaints in general, and burning and itching in particular, occurred less frequently in the terconazole vaginal cream 0.8% 3 day regimen (5% vs. 6%-9% with placebo). Other adverse experiences reported with terconazole vaginal cream 0.8% were abdominal pain (3.4% vs. 1% with placebo) and fever (1% vs. 0.3% with placebo). The therapy-related dropout rate was 2.0% for the terconazole vaginal cream 0.8%. The adverse drug experience most frequently causing discontinuation of therapy was vulvovaginal itching, 0.7% with the terconazole vaginal cream 0.8% group and 0.3% with the placebo group.

OVERDOSAGE

Overdosage of terconazole in humans has not been reported to date. In the rat, the oral LD 50 values were found to be 1741 and 849 mg/kg for the male and female, respectively. The oral LD 50 values for the male and female dog were &ap;1280 and ≥640 mg/kg, respectively.

DOSAGE AND ADMINISTRATION

One full applicatorful (5 g) of terconazole vaginal cream 0.8% (40 mg terconazole) should be administered intravaginally once daily at bedtime for three consecutive days. Before prescribing another course of therapy, the diagnosis should be reconfirmed by smears and/or cultures and other pathogens commonly associated with vulvovaginitis ruled out. The therapeutic effect of terconazole vaginal cream 0.8% is not affected by menstruation.

HOW SUPPLIED

Product: 50090-6299

NDC: 50090-6299-0 20 g in a TUBE, WITH APPLICATOR

Terconazole Vaginal Cream 0.8% PATIENT INSTRUCTIONS 3- DAY THERAPY

Filling the applicator:

1. Remove the cap from the tube.
2. Use the pointed tip on the top of the cap to puncture the seal on the tube.
3. Screw the applicator onto the tube.
4. Squeeze the tube from the bottom and fill the applicator until the plunger stops.
5. Unscrew the applicator from the tube.

Using the applicator:

1. Lie on your back with your knees drawn up toward your chest.
2. Holding the applicator by the ribbed end of the barrel, insert the filled applicator into the vagina as far as it will comfortably go.
3. Slowly press the plunger of the applicator to release the cream into the vagina.
4. Remove the applicator from the vagina.
5. Apply one applicatorful each night for as many days at bedtime, as directed by your doctor.

Cleaning the applicator:

After each use, you should thoroughly clean the applicator by following the procedure below:

1. Pull the plunger out of the barrel.
2. Wash the pieces with lukewarm, soapy water, and dry them thoroughly.
3. Put the applicator back together by gently pushing the plunger into the barrel as far as it will go.

NOTE: Store at 20°C to 25°C (68°F to 77°F), excursions permitted 15°C to 30°C (59°F to 86°F). [See USP Controlled Room Temperature].

See end flap for lot number and expiration date.

A WORD ABOUT YEAST INFECTIONS

Why do yeast infections occur?

Yeast infections are caused by an organism called Candida (KAN di duh). It may be present in small and harmless amounts in the mouth, digestive tract, and vagina. Sometimes the natural balance of the vagina becomes upset. This may lead to rapid growth of Candida, which results in a yeast infection. Symptoms of a yeast infection include itching, burning, redness, and an abnormal discharge.

Your doctor can make the diagnosis of a yeast infection by evaluating your symptoms and looking at a sample of the discharge under the microscope.

How can I prevent yeast infections?

Certain factors may increase your chance of developing a yeast infection. These factors don't actually cause the problem, but they may create a situation that allows the yeast to grow rapidly.

- Clothing: Tight jeans, nylon underwear, pantyhose, and wet bathing suits can hold in heat and moisture (two conditions in which yeast organisms thrive). Looser pants or skirts, 100% cotton underwear, and stockings may help avoid this problem.
- Diet: Cutting down on sweets, milk products, and artificial sweeteners may reduce the risk of yeast infections.
- Antibiotics: Antibiotics work by eliminating disease-causing organisms. While they are helpful in curing other problems, antibiotics may lead to an overgrowth of Candida in the vagina.
- Pregnancy: Hormonal changes in the body during pregnancy encourage the growth of yeast. This is a very common time for an infection to occur. Until the baby is born, it may be hard to completely eliminate yeast infections. If you believe you are pregnant, tell your doctor.
- Menstruation: Sometimes monthly changes in hormone levels may lead to yeast infections.
- Diabetes: In addition to heat and moisture, yeast thrives on sugar. Because diabetics often have sugar in their urine, their vaginas are rich in this substance. Careful control of diabetes may help prevent yeast infections.
Controlling these factors can help eliminate yeast infections and may prevent them from coming back.

Some other helpful tips:

1. For best results, be sure to use the medication as prescribed by your doctor, even if you feel better very quickly.
2. Avoid sexual intercourse, if your doctor advises you to do so.
3. If your partner has any penile itching, redness, or discomfort, he should consult his physician and mention that you are being treated for a yeast infection.
4. You can use the medication even if you are having your menstrual period. However, you should not use tampons because they may absorb the medication. Instead, use external pads or napkins until you have finished your medication. You may also wish to wear a sanitary napkin if the vaginal medication leaks.
5. Dry the genital area thoroughly after showering, bathing, or swimming. Change out of a wet bathing suit or damp exercise clothes as soon as possible. A dry environment is less likely to encourage the growth of yeast.
6. Wipe from front to rear (away from the vagina) after a bowel movement.
7. Don't douche unless your doctor specifically tells you to do so. Douching may disturb the vaginal balance.
8. Don't scratch if you can help it. Scratching can cause more irritation and spread the infection.
9. Discuss with your physician any medication you are already taking. Certain types of medication can make your vagina more susceptible to infection.
10. Eat nutritious meals to promote your general health.
E. FOUGERA & CO.
  A division of Fougera Pharmaceuticals Inc.
  Melville, New York 11747

46270465A

R05/2020